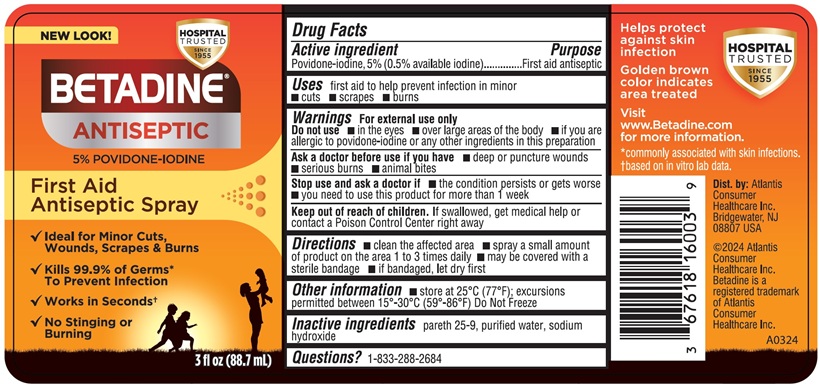 DRUG LABEL: Betadine
NDC: 67618-192 | Form: SPRAY
Manufacturer: Atlantis Consumer Healthcare, Inc.
Category: otc | Type: HUMAN OTC DRUG LABEL
Date: 20250102

ACTIVE INGREDIENTS: POVIDONE-IODINE 5 mg/1 mL
INACTIVE INGREDIENTS: C12-15 Pareth-9; Water; Sodium Hydroxide

BETADINE® Spray
5% Povidone-iodine

Drug Facts

Active ingredients

Povidone-iodine, 5% (0.5% available iodine)

Purpose

First aid Antiseptic

Uses

First aid to help prevent infection in minor

- cuts
- scrapes
- burns

Warnings

For external use only

Do not use

- in the eyes
- over large areas of the body
- If you are allergic to povidone-iodine or any other ingredients in this preparation

Ask a doctor before use if you have

- deep or puncture wounds
- serious burns
- animal bites

Stop use and ask a doctor if

- the condition persists or gets worse
- you need to use this product for more than 1 week

Keep out of reach of children

If swallowed, get medical help or contact a Poison Control Center right away.

Directions

- clean the affected area
- spray a small amount of the product on the area 1 to 3 times daily
- may be covered with a sterile bandage
- if bandaged, let dry first

Other information

- store at 25⁰C (77⁰F); excursions permitted between 15⁰-30⁰C (59⁰-86⁰F) Do Not Freeze

Inactive ingredients

pareth 25-9, purified water, sodium hydroxide

Questions?

1-833-288-2684

PACKAGE LABEL.PRINCIPAL DISPLAY PANEL

NEW LOOK!
HOSPITAL
TRUSTED
SINCE
1955
BETADINE®
ANTISEPTIC
5% POVIDONE-IODINE
First Aid
Antiseptic Spray
√ Ideal for Minor Cuts, Wounds, Scrapes & Burns
√ Kills 99.9% of Germs* To Prevent Infection
√ Works in Secondst
√ No Stinging or Burning
3 fl oz (88.7mL)

Helps protect
against skin
infection
Golden brown
color indicates
area treated
Visit
www.Betadine.com
for more information
*commonlly associated with skin infections.
tbased on in vitro lab data.
Dist. by: Atlantis
Consumer
Healthcare Inc.
Bridgewater, NJ
08807 USA
©2024 Atlantis
Consumer
Healthcare Inc.
Betadine is a
registered trademark
of Atlantis
Consumer
Healthcare Inc.
A0324